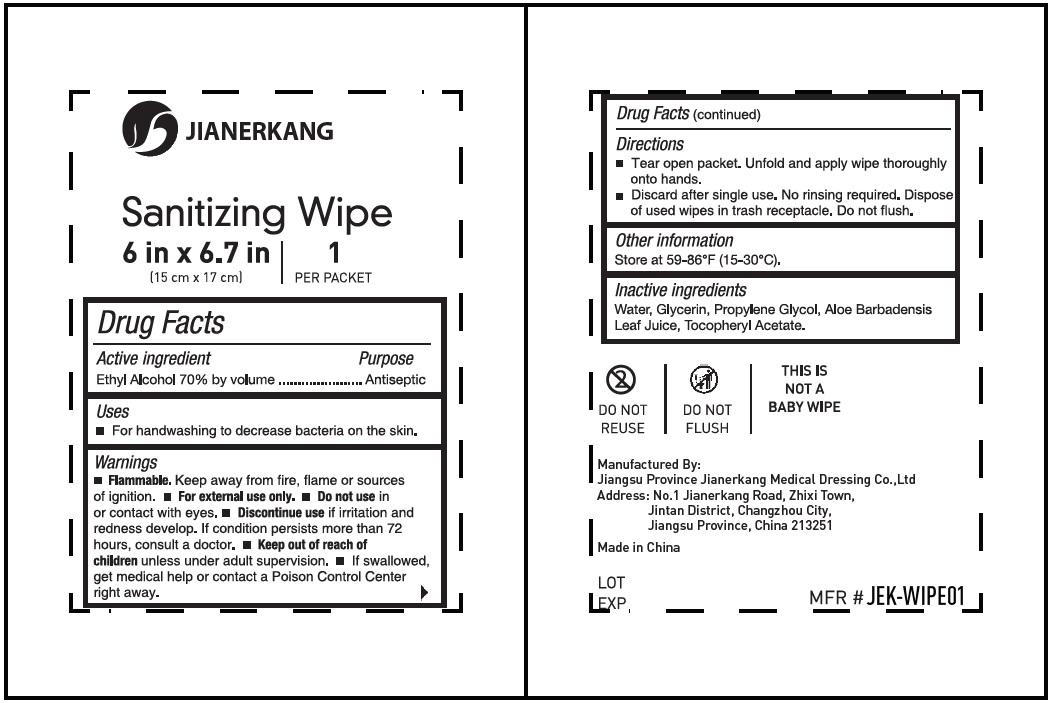 DRUG LABEL: Jianerkang Sanitizing Wipe
NDC: 34645-0003 | Form: CLOTH
Manufacturer: Jianerkang Medical Co., Ltd
Category: otc | Type: HUMAN OTC DRUG LABEL
Date: 20231023

ACTIVE INGREDIENTS: ALCOHOL 0.7 mL/1 mL
INACTIVE INGREDIENTS: WATER; GLYCERIN; PROPYLENE GLYCOL; ALOE VERA LEAF; .ALPHA.-TOCOPHEROL ACETATE

Jianerkang Sanitizing Wipe

Active Ingredients

Ethyl Alcohol 70% by volume

Purpose

Antiseptic

Use

For handwashing to decrease bacteria on the skin.

Warnings

- Keep away from fire, flame or sources of ignition. Flammable.
- For external use only.

Do not use

- in or contact with eyes.

Discontinue use

if irritation and redness develop. If condition persists more than 72 hours, consult a doctor.

Keep out of reach of children.

unless under adult supervision.

- If swallowed, get medical help or contact a Poison Control Center right away.

Directions

- Tear open packet. Unfold and apply wipe thoroughly onto hands.
- Discard after single use. No rinsing required. Dispose of used wipes in trash receptacle. Do not flush.

Other Information

Store at 59°-86°F (15°-30°C).

Inactive Ingredient

Water, Glycerin, Propylene Glycol, Aloe Barbadensis Leaf Juice, Tocopheryl Acetate.